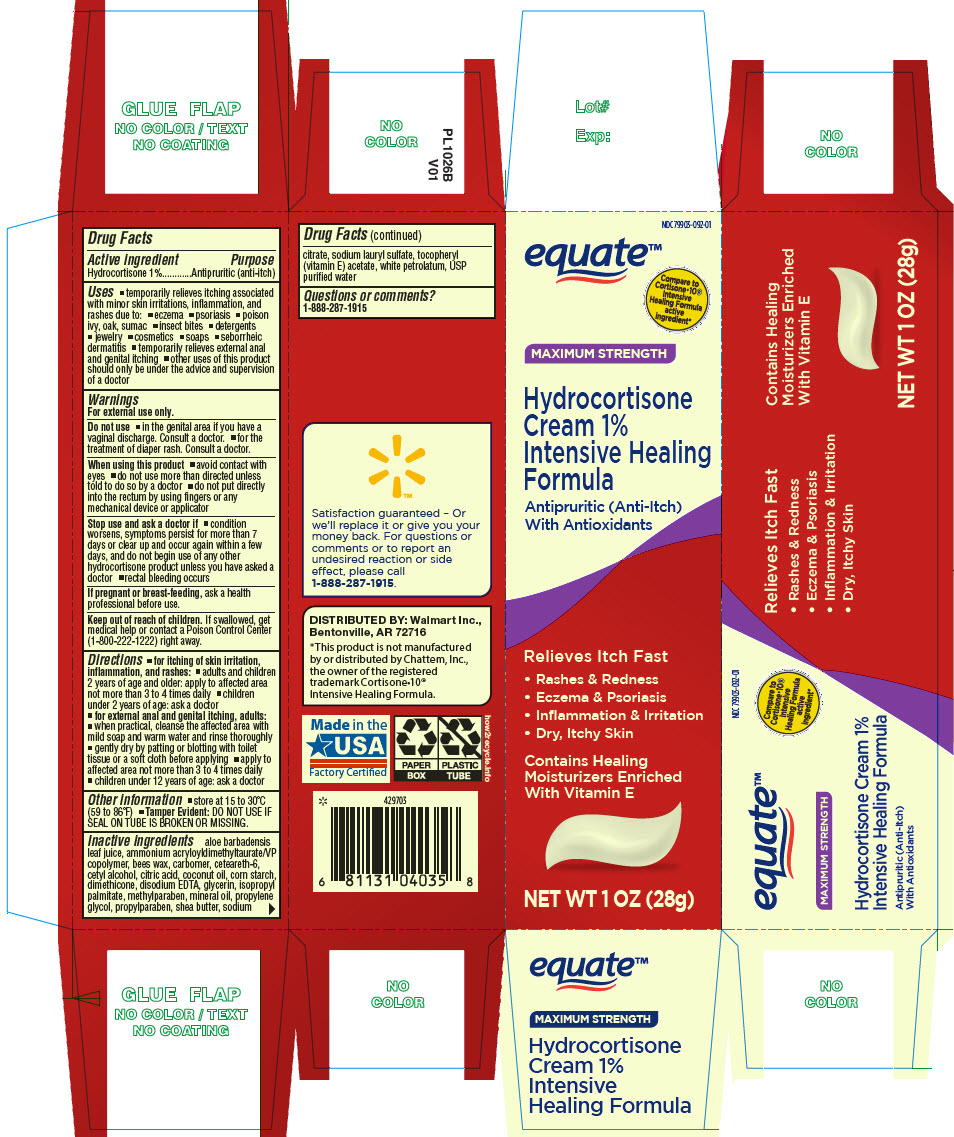 DRUG LABEL: Equate Hydrocortisone
NDC: 79903-092 | Form: CREAM
Manufacturer: WalMart
Category: otc | Type: HUMAN OTC DRUG LABEL
Date: 20250116

ACTIVE INGREDIENTS: Hydrocortisone 10 mg/1 g
INACTIVE INGREDIENTS: ALOE VERA LEAF; ammonium acryloyldimethyltaurate/VP copolymer; YELLOW WAX; CARBOMER HOMOPOLYMER, UNSPECIFIED TYPE; ceteareth-6; cetyl alcohol; CITRIC ACID MONOHYDRATE; coconut oil; STARCH, CORN; dimethicone; EDETATE DISODIUM ANHYDROUS; glycerin; isopropyl palmitate; methylparaben; mineral oil; propylene glycol; propylparaben; shea butter; sodium

Equate™ Hydrocortisone Cream 1% Intensive Healing Formula
Topical

Drug Facts

Active ingredient

Hydrocortisone 1%

Purpose

Antipruritic (anti-itch)

Uses

- temporarily relieves itching associated with minor skin irritations, inflammation, and rashes due to:
  - eczema
  - psoriasis
  - poison ivy, oak, sumac
  - insect bites
  - detergents
  - jewelry
  - cosmetics
  - soaps
  - seborrheic dermatitis
- temporarily relieves external anal and genital itching
- other uses of this product should only be under the advice and supervision of a doctor

Warnings

For external use only.

Do not use

- in the genital area if you have a vaginal discharge. Consult a doctor.
- for the treatment of diaper rash. Consult a doctor.

When using this product

- avoid contact with eyes
- do not use more than directed unless told to do so by a doctor
- do not put directly into the rectum by using fingers or any mechanical device or applicator

Stop use and ask a doctor if

- condition worsens, symptoms persist for more than 7 days or clear up and occur again within a few days, and do not begin use of any other hydrocortisone product unless you have asked a doctor
- rectal bleeding occurs

PREGNANCY OR BREAST FEEDING

If pregnant or breast-feeding, ask a health professional before use.

Keep out of reach of children. If swallowed, get medical help or contact a Poison Control Center (1-800-222-1222) right away.

Directions

- for itching of skin irritation, inflammation, and rashes:
  - adults and children 2 years of age and older: apply to affected area not more than 3 to 4 times daily
  - children under 2 years of age: ask a doctor
- for external anal and genital itching, adults:
  - when practical, cleanse the affected area with mild soap and warm water and rinse thoroughly
  - gently dry by patting or blotting with toilet tissue or a soft cloth before applying
  - apply to affected area not more than 3 to 4 times daily
  - children under 12 years of age: ask a doctor

Other information

- store at 15 to 30°C (59 to 86°F)
- Tamper Evident: DO NOT USE IF SEAL ON TUBE IS BROKEN OR MISSING.

Inactive ingredients

aloe barbadensis leaf juice, ammonium acryloyldimethyltaurate/VP copolymer, bees wax, carbomer, ceteareth-6, cetyl alcohol, citric acid, coconut oil, corn starch, dimethicone, disodium EDTA, glycerin, isopropyl palmitate, methylparaben, mineral oil, propylene glycol, propylparaben, shea butter, sodium citrate, sodium lauryl sulfate, tocopheryl (vitamin E) acetate, white petrolatum, USP purified water

Questions or comments?

1-888-287-1915

DISTRIBUTED BY: Walmart Inc.,
Bentonville, AR 72716

PRINCIPAL DISPLAY PANEL - 28 g Tube Carton

NDC 79903-092-01

equate™

Compare to
Cortisone•10®
Intensive
Healing Formula
active
ingredient*

MAXIMUM STRENGTH

Hydrocortisone
Cream 1%
Intensive Healing
Formula

Antipruritic (Anti-Itch)
With Antioxidants

Relieves Itch Fast

- Rashes & Redness
- Eczema & Psoriasis
- Inflammation & Irritation
- Dry, Itchy Skin

Contains Healing
Moisturizers Enriched
With Vitamin E

NET WT 1 OZ (28g)